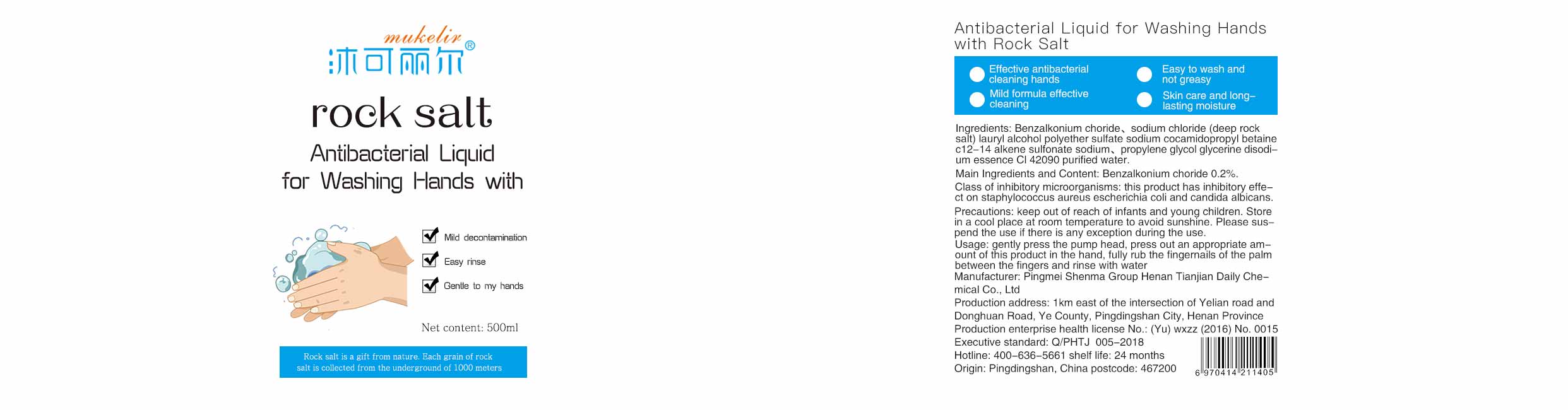 DRUG LABEL: Mukelir Antibacterial Liquid for Washing Hands with Rock Salt
NDC: 76620-002 | Form: GEL
Manufacturer: Pingmei Shenma Group Henan Tianjian Daily Chemical Co., Ltd.
Category: otc | Type: HUMAN OTC DRUG LABEL
Date: 20200512

ACTIVE INGREDIENTS: BENZALKONIUM CHLORIDE 0.2 g/100 mL
INACTIVE INGREDIENTS: COCAMIDOPROPYL BETAINE; EDETATE DISODIUM; GLYCERIN; SODIUM LAURYL SULFATE; SODIUM CHLORIDE; WATER; PROPYLENE GLYCOL; SODIUM C14 OLEFIN SULFONATE; ACACIA SENEGAL FLOWER

Mukelir Antibacterial Liquid for Washing Hands with Rock Salt

Active Ingredient(s)

0.20% Benzalkonium choride Purpose: Antiseptic

Purpose

Antiseptic, Hand Sanitizer

Use

The product is a topical product, which is suitable for cleaning and bacteriostasis of hand skin.

Warnings

Please suspend the use if there is any exception during the use.

Keep out of reach of infnants and young children.

Do not use

Please suspend the use if there is any exception during the use.

WHEN USING

Keep out of reach of infnants and young children.

STOP USE

Please suspend the use if there is any exception during the use.

KEEP OUT OF REACH OF CHILDREN

Keep out of reach of infnants and young children.

Directions

gently press the pump head, press out an appropriate amount of this product in the hand, fully rub the fingernails of palm between the fingers and rinse with water

Other information

Store in a cool place at room temperature to avoid sunshine.

Inactive ingredients

Sodium chloride, Sodium lauryl sulfate, Cocamidopropyl Betaine, C12-14 Sodium olefin sulfonate, Benzalkonium choride, Propylene glycol, glycerin, EDTA Disodium, essence, CL42090, purified water

Package Label - Principal Display Panel

500 mL NDC: 76620-002-01